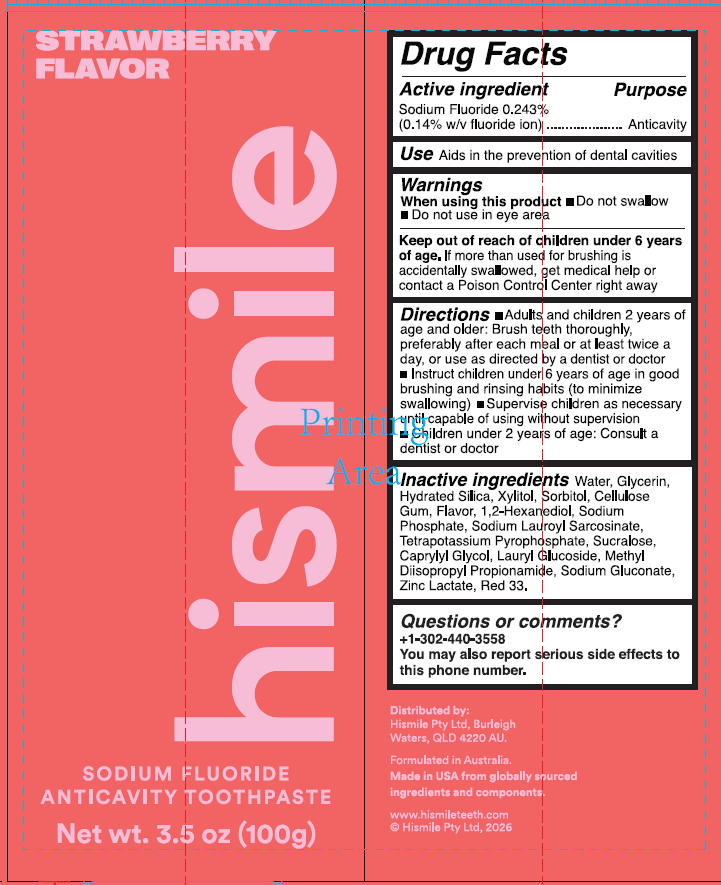 DRUG LABEL: Strawberry Flavor Sodium Fluoride Anticavity Toothpast
NDC: 83013-339 | Form: GEL
Manufacturer: HISMILE PTY LTD
Category: otc | Type: HUMAN OTC DRUG LABEL
Date: 20251102

ACTIVE INGREDIENTS: SODIUM FLUORIDE 0.243 g/100 g
INACTIVE INGREDIENTS: CAPRYLYL GLYCOL; METHYL DIISOPROPYL PROPIONAMIDE; 1,2-HEXANEDIOL; CELLULOSE GUM; SODIUM LAUROYL SARCOSINATE; RED 33; XYLITOL; SODIUM PHOSPHATE; LAURYL GLUCOSIDE; WATER; ZINC LACTATE; GLYCERIN; HYDRATED SILICA; SUCRALOSE; SORBITOL; TETRAPOTASSIUM PYROPHOSPHATE; SODIUM GLUCONATE

Strawberry Flavor Sodium Fluoride Anticavity Toothpaste

Active ingredient

Sodium Fluoride 0.243%

(0.14% w/v fluoride ion)

Purpose

Anticavity

Use

Aids in the prevention of dental cavities.

Warnings

When using this product

- Do not swallow
- Do not use in eye area

Keep out of reach of children under 6 years

If more than used for brushing is accidentally swallowed, get medical help or contact a Poison Control Center right away.

Directions

- Adults and children 2 years of age and older: Brush teeth thoroughly, preferably after each meal or at least twice a day, or use as directed by a dentist or doctor.
- Instruct children under 6 years of age in good brushing and rinsing habits (to minimize swallowing).
- Supervise children as necessary until capable of using without supervision.
- Children under 2 years of age: Consult a dentist or doctor.

Inactive ingredients

Water

Glycerin

Hydrated Silica

Xylitol

Sorbitol

Cellulose Gum

Flavor

1,2-Hexanediol

Sodium Phosphate

Sodium Lauroyl Sarcosinate

Tetrapotassium Pyrophosphate

Sucralose

Caprylyl Glycol

Lauryl Glucoside

Methyl Diisopropyl Propionamide

Sodium Gluconate

Zinc Lactate

Red 33